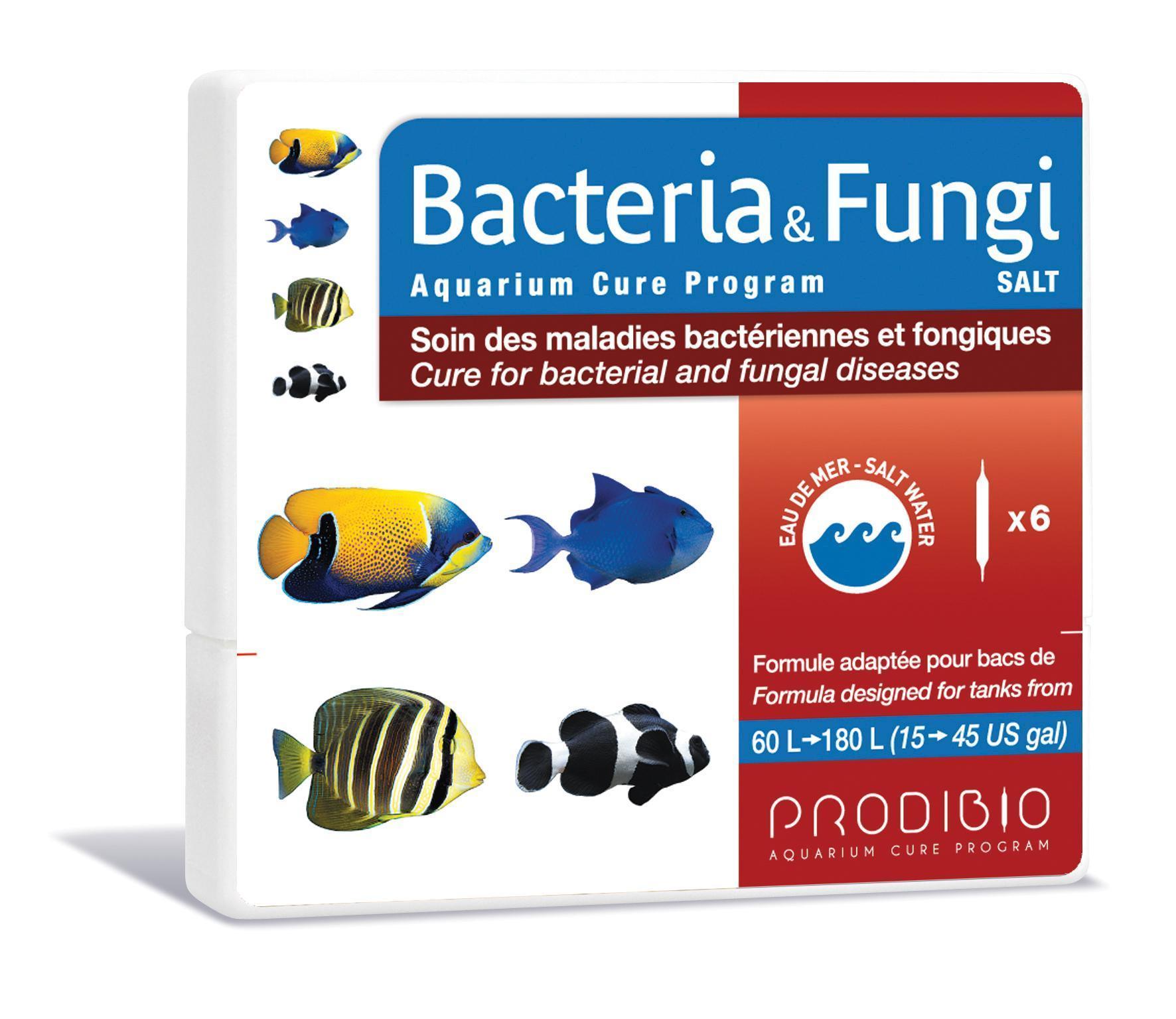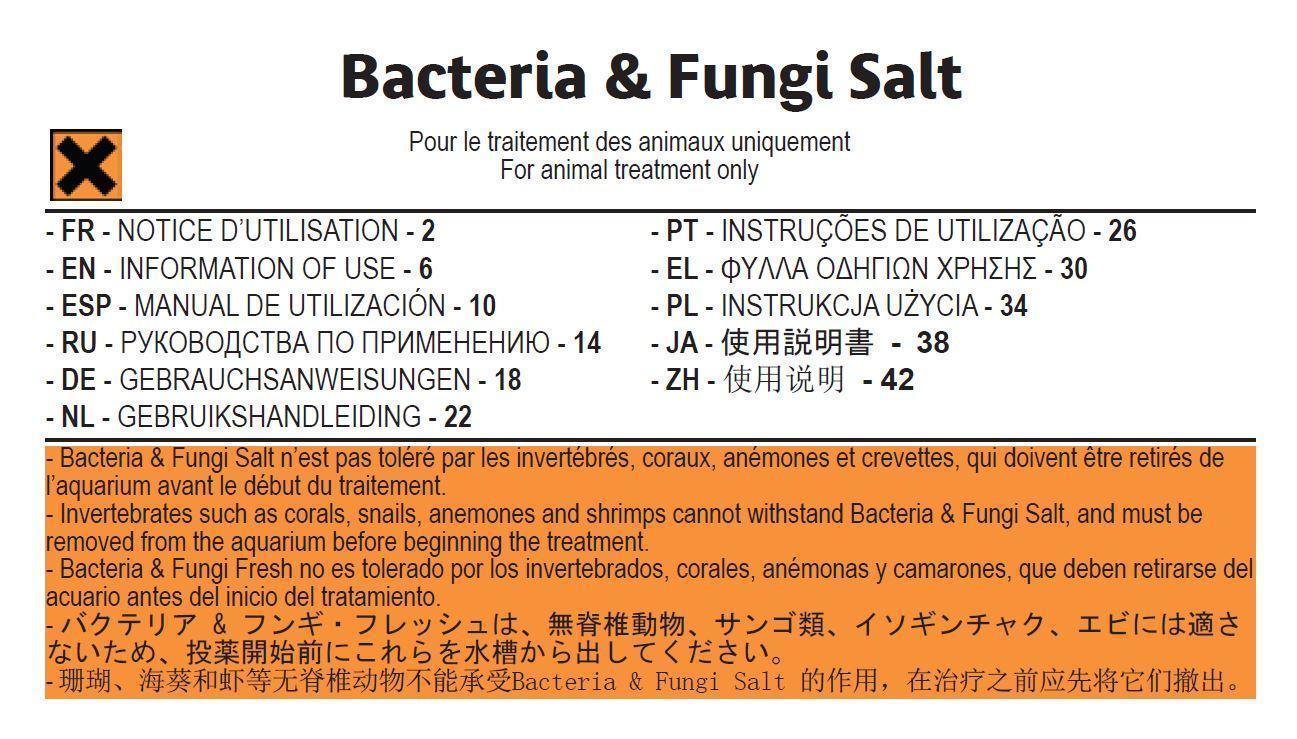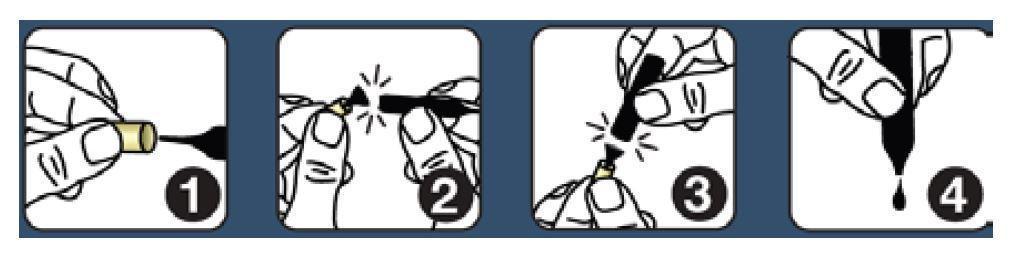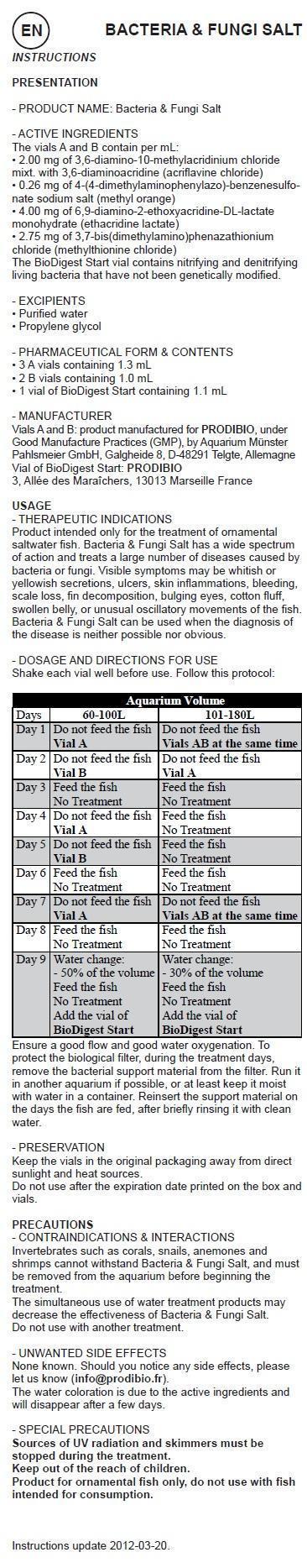 DRUG LABEL: BACTERIA and FUNGI Aquarium Cure Program Salt
NDC: 86048-010 | Form: KIT | Route: ORAL
Manufacturer: Prodibio SAS
Category: animal | Type: OTC ANIMAL DRUG LABEL
Date: 20150903

ACTIVE INGREDIENTS: ACRIFLAVINE HYDROCHLORIDE 2.00 mg/1 mL; METHYL ORANGE 0.26 mg/1 mL; ethacridine lactate 4.00 mg/1 mL; METHYLENE BLUE ANHYDROUS 2.75 mg/1 mL; ACRIFLAVINE HYDROCHLORIDE 2.00 mg/1 mL; methyl orange 0.26 mg/1 mL; ethacridine lactate 4.00 mg/1 mL; METHYLENE BLUE ANHYDROUS 2.75 mg/1 mL
INACTIVE INGREDIENTS: WATER; PROPYLENE GLYCOL; WATER; PROPYLENE GLYCOL

BACTERIA & FUNGI Aquarium Cure Program Salt

- PRODUCT NAME: Bacteria & Fungi Salt

- ACTIVE INGREDIENTS

The vials A and B contain per mL:
• 2.00 mg of 3,6-diamino-10-methylacridinium chloride mixt. with 3,6-diaminoacridine (acriflavine chloride)
• 0.26 mg of 4-(4-dimethylaminophenylazo)-benzenesulfonate sodium salt (methyl orange)
• 4.00 mg of 6,9-diamino-2-ethoxyacridine-DL-lactate monohydrate (ethacridine lactate)
• 2.75 mg of 3,7-bis(dimethylamino)phenazathionium chloride (methylthionine chloride)
The BioDigest Start vial contains nitrifying and denitrifying living bacteria that have not been genetically modified.

- EXCIPIENTS

• Purified water
• Propylene glycol

- PHARMACEUTICAL FORM & CONTENTS

• 3 A vials containing 1.3 mL
• 2 B vials containing 1.0 mL
• 1 vial of BioDigest Start containing 1.1 mL

- MANUFACTURER

Vials A and B : product manufactured for PRODIBIO,
under GMP, by Aquarium Münster Pahlsmeier GmbH,
Galgheide 8, D-48291 Telgte, GE
Vial of BioDigest Start : PRODIBIO
3, Allée des Maraîchers, 13013 Marseille, France

USAGE

- THERAPEUTIC INDICATIONS
Product intended only for the treatment of ornamental saltwater fish. Bacteria & Fungi Salt has a wide spectrum of action and treats a large number of diseases caused by bacteria or fungi. Visible symptoms may be whitish or yellowish secretions, ulcers, skin inflammations, bleeding, scale loss, fin decomposition, bulging eyes, cotton fluff, swollen belly, or unusual oscillatory movements of the fish. Bacteria & Fungi Salt can be used when the diagnosis of the disease is neither possible nor obvious.

- DOSAGE AND DIRECTIONS FOR USE

Shake each vial well before use. Follow this protocol:

Days | 60-100L | 101-180L
Day 1 | Do not feed the fish Vial A | Do not feed the fish Vials AB together
Day 2 | Do not feed the fish; Vial B | Do not feed the fish Vials A
Day 3 | Feed the fish No Treatment | Feed the fish No Treatment
Day 4 | Do not feed the fish Vial A | Feed the fish No Treatment
Day 5 | Do not feed the fish; Vial B | Feed the fish No Treatment
Day 6 | Feed the fish No Treatment | Feed the fish No Treatment
Day 7 | Do not feed the fish Vial A | Do not feed the fish; Vials AB at the same time
Day 8 | Feed the fish No Treatment | Feed the fish No Treatment
Day 9 | Water change: -50% of the volume; Feed the fish; No Treatment Add the vial of; BioDigest Start | Water Change:; -30% of the volume Feed the fish; No Treatment; Add the vial of BioDigest Start

Ensure a good flow and good water oxygenation. To protect the biological filter, during the treatment days, remove the bacterial support material from the filter. Run it in another aquarium if possible, or at least keep it moist with water in a container. Reinsert the support material on the days the fish are fed, after briefly rinsing it with clean water.

- PRESERVATION

Keep the vials in the original packaging away from direct sunlight and heat sources.
Do not use after the expiration date printed on the box and vials.

PRECAUTIONS - CONTRAINDICATIONS & INTERACTIONS

Invertebrates such as corals, snails, anemones and shrimps cannot withstand Bacteria & Fungi Salt, and must be removed from the aquarium before beginning the treatment. The simultaneous use of water treatment products may decrease the effectiveness of Bacteria & Fungi Salt. Do not use with another treatment.

- UNWANTED SIDE EFFECTS

None known. Should you notice any side effects, please let us know (info@prodibio.fr).
The water coloration is due to the active ingredients and will disappear after a few days.

- SPECIAL PRECAUTIONS

Sources of UV radiation and skimmers must be stopped during the treatment.
Product for ornamental fish only, do not use with fish intended for consumption.

This veterinary medicines is marketed in accordinance with the Small Animal Exception Scheme

Instructions update 2012-08.

- Special precautions for the disposal of unused pharmaceuticals

Dispose old drugs not entirely used up at the respective collecting points

Disposal advice: after use, vials must be thrown in recyclable glass rubbish